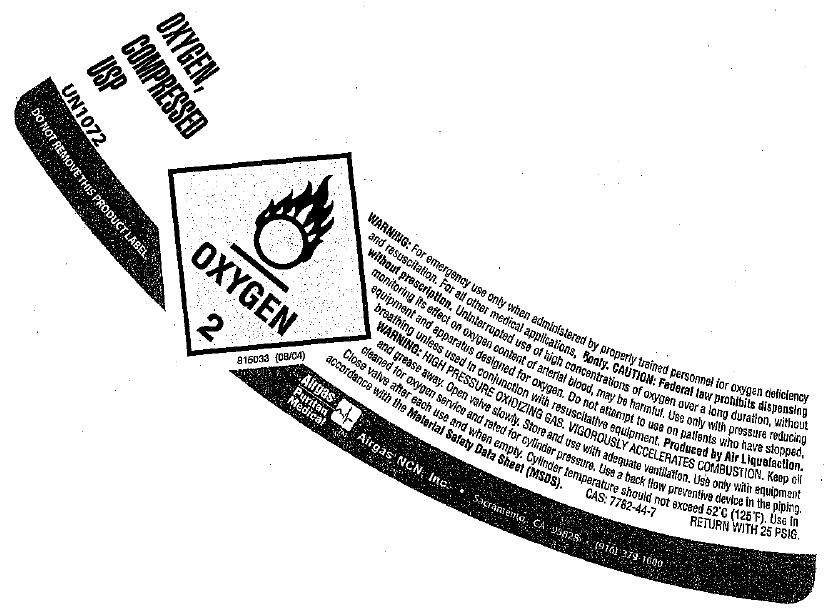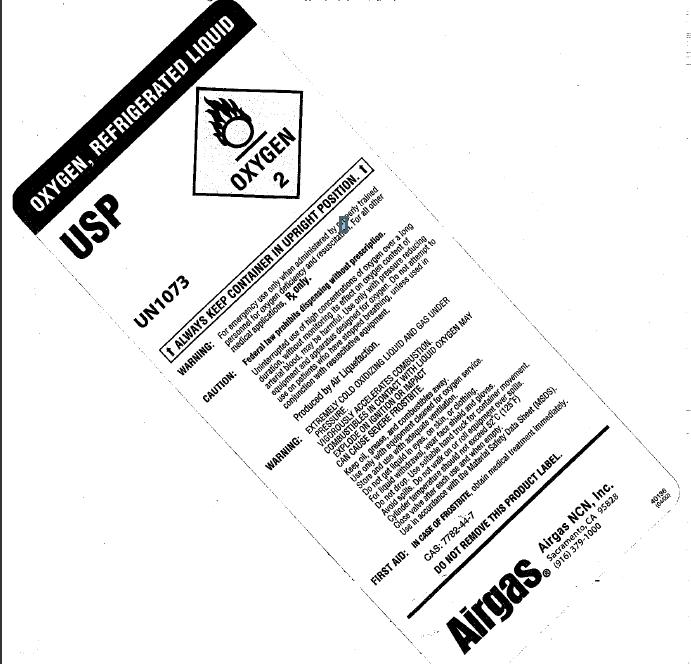 DRUG LABEL: Oxygen
NDC: 58789-001 | Form: GAS
Manufacturer: Airgas Northern California and Nevada, Inc.
Category: prescription | Type: HUMAN PRESCRIPTION DRUG LABEL
Date: 20100402

ACTIVE INGREDIENTS: Oxygen 992 mL/1 L

oxygen

PACKAGE LABEL

OXYGEN, COMPRESSED USP UN1072
DO NOT REMOVE THIS PRODUCT LABEL
WARNING: For emergency use only when adminstrered by properly trained personnel for oxygen deficiency and resuscitation. For all other medical applications, Rx only. CAUTION: Federal law prohibits dispensing without prescription. Uninterrupted use of high concentrations of oxygen over a long duration, without monitoring its effect on oxygen content of arterial blood, may be harmful. Use only with pressure reducing equipment and apparatus designed for oxygen. Do not attempt to use on patients who have stopped breathing unless used in conjunction with resuscitative equipment. Produced with Air Liquefaction. WARNING: HIGH PRESSURE OXIDIZING GAS. VIGOROUSLY ACCELERATES CONSUMPTION. Keep oil and grease away. Open valve slowly. Store and use with adequate ventilation. Use only with equipment cleaned for oxygen service and rated for cylinder pressure. Use a back flow preventive device in the piping. Close valve after each use and when empty. Cylinder temperature should not exceed 52C(125F). Use in accordance with the Material Safety Data Sheets (MSDS). CAS 7782-44-7 RETURN WITH 25 PSIG
Airgas Puritan Medical Airgas NCN, Inc. Sacramento, CA 95828 (916)379-1000
816033 (08/04)

PACKAGE LABEL

Oxygen, Refrigerated Liquid
USP Oxygen 2
UN 1073
ALWAYS KEEP CONTAINER IN UPRIGHT POSITION
WARNING: For emergency use only when administered by properly trained personnel for oxygen deficiency and resuscitation. For all other medical applications, Rx Only.
CAUTION: Federal law prohibits dispensing without prescription. Uninterrupted use of high concentrations of oxygen over a long duration, without monitoring its effect on oxygen content of arterial blood, may be harmful. Use only with pressure reducing equipment and apparatus designed for oxygen. Do not attempt to use on patients who have stopped breathing, unless in conjunction with resuscitative equipment.
Produced by Air Liquefaction.
WARNING: EXTREMELY COLD OXIDIZING LIQUID AND GAS UNDER PRESSURE. VIGOROUSLY ACCELERATES COMBUSTION. COMBUSTIBLES IN CONTACT WITH LIQUID OXYGEN MAY EXPLODE ON IGNITION OR IMPACT. CAN CAUSE SEVERE FROSTBITE.
Keep oil, grease, and combustibles away. Use only with equipment cleaned for oxygen service. Store and use with adequate ventilation. Do not get liquid in eyes, on skin, or clothing. For liquid withdrawal, wear face shield and gloves. Do not drop. Use suitable hand truck for container movement. Avoid spills. Do not walk on or roll equipment over spills. Cylinder temperature should not exceed 52 C(125F) Close valve after each use and when empty. Use in accordance with Material Safety Data Sheet (MSDS).
FIRST AID: IN CASE OF FROSTBITE, obtain medical treatment immediately.
CAS: 7782-44-7
DO NOT REMOVE THIS PRODUCT LABEL.
Airgas Airgas NCN, Inc. Sacramento, CA 95828 (916) 379-1000
40136 (04/02)